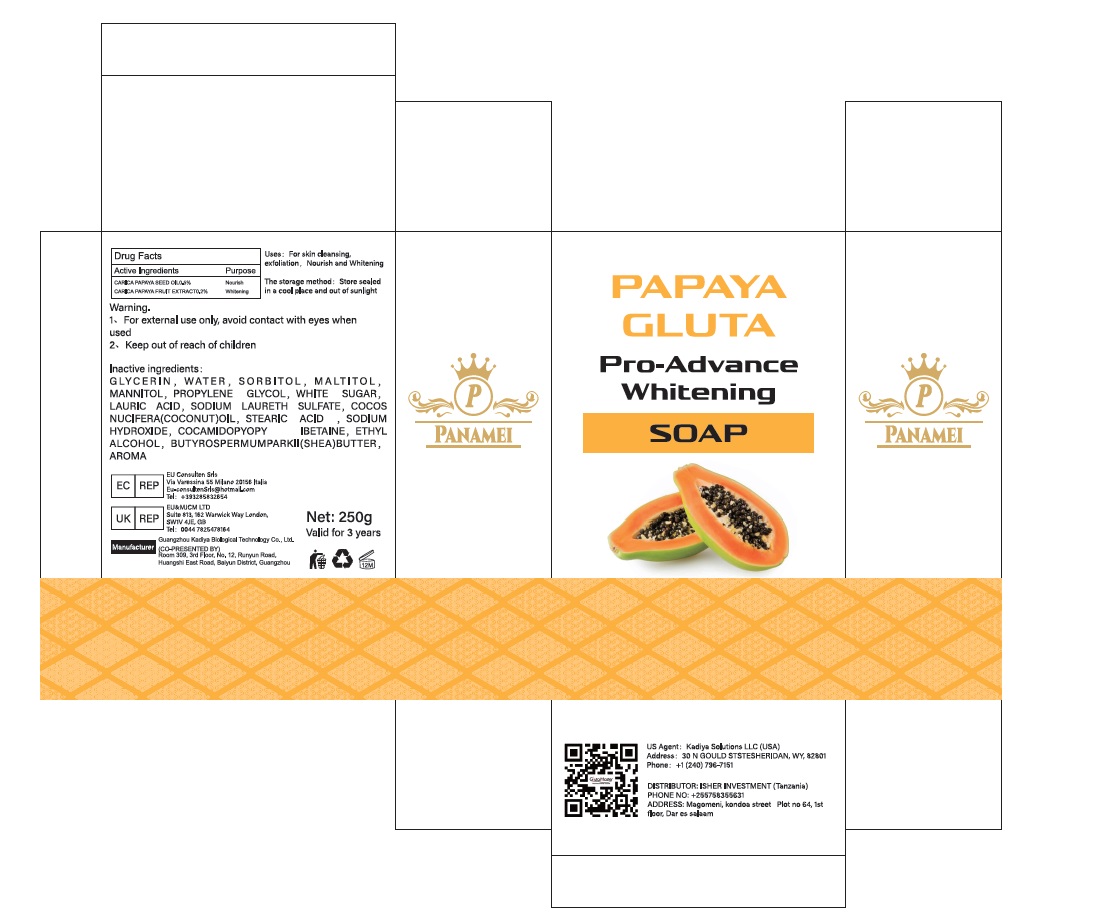 DRUG LABEL: PAPAYA GLUTASOAP
NDC: 84423-077 | Form: SOAP
Manufacturer: Guangzhou Kadiya Biotechnology Co., Ltd.
Category: otc | Type: HUMAN OTC DRUG LABEL
Date: 20250218

ACTIVE INGREDIENTS: PAPAYA SEED OIL 1.25 g/250 g; CARICA PAPAYA (PAPAYA) FRUIT 0.5 g/250 g
INACTIVE INGREDIENTS: WATER; COCOS NUCIFERA (COCONUT) OIL; LAURIC ACID; STEARIC ACID; SORBITOL; GLYCERIN; BUTYROSPERMUM PARKII (SHEA) BUTTER; MANNITOL; PROPYLENE GLYCOL; SODIUM LAURETH SULFATE; MALTITOL; SODIUM HYDROXIDE; SUCROSE; COCAMIDOPROPYL BETAINE

PURPOSE

For skin cleansing, exfoliation，Nourish and Whitening

INACTIVE INGREDIENT

GLYCERIN，WATER，SORBITOL，MALTITOL，MANNITOL，PROPYLENE GLYCOL，WHITE SUGAR，LAURIC ACID，SODIUM LAURETH SULFATE，COCOS NUCIFERA(COCONUT)OIL，STEARIC ACID ，SODIUM HYDROXIDE，COCAMIDOPYOPY IBETAINE，ETHYL ALCOHOL，BUTYROSPERMUMPARKII(SHEA)BUTTER，AROMA

Warning.
1、For external use only, avoid contact with eyes when used
2、Keep out of reach of children

INDICATIONS AND USAGE

For skin cleansing,exfoliation, Nourish and Whitening

DOSAGE AND ADMINISTRATION

Wet yourself in the shower and lather up

KEEP OUT OF REACH OF CHILDREN SECTION

Active Ingredients
CARICA PAPAYA SEED OIL0.5%
CARICA PAPAYA FRUIT EXTRACT0.2%

PACKAGE LABEL

Active Ingredients
CARICA PAPAYA SEED OIL 0.5%
CARICA PAPAYA FRUIT EXTRACT 0.2%

Uses：
For skin cleansing, exfoliation，Nourish and Whitening

The storage method：
Store sealed in a cool place and out of sunlight

Warning.
1、For external use only, avoid contact with eyes when used
2、Keep out of reach of children

Inactive ingredients：
GLYCERIN，WATER，SORBITOL，MALTITOL，MANNITOL，PROPYLENE GLYCOL，WHITE SUGAR，LAURIC ACID，SODIUM LAURETH SULFATE，COCOS NUCIFERA(COCONUT)OIL，STEARIC ACID ，SODIUM HYDROXIDE，COCAMIDOPYOPY IBETAINE，ETHYL ALCOHOL，BUTYROSPERMUMPARKII(SHEA)BUTTER，AROMA